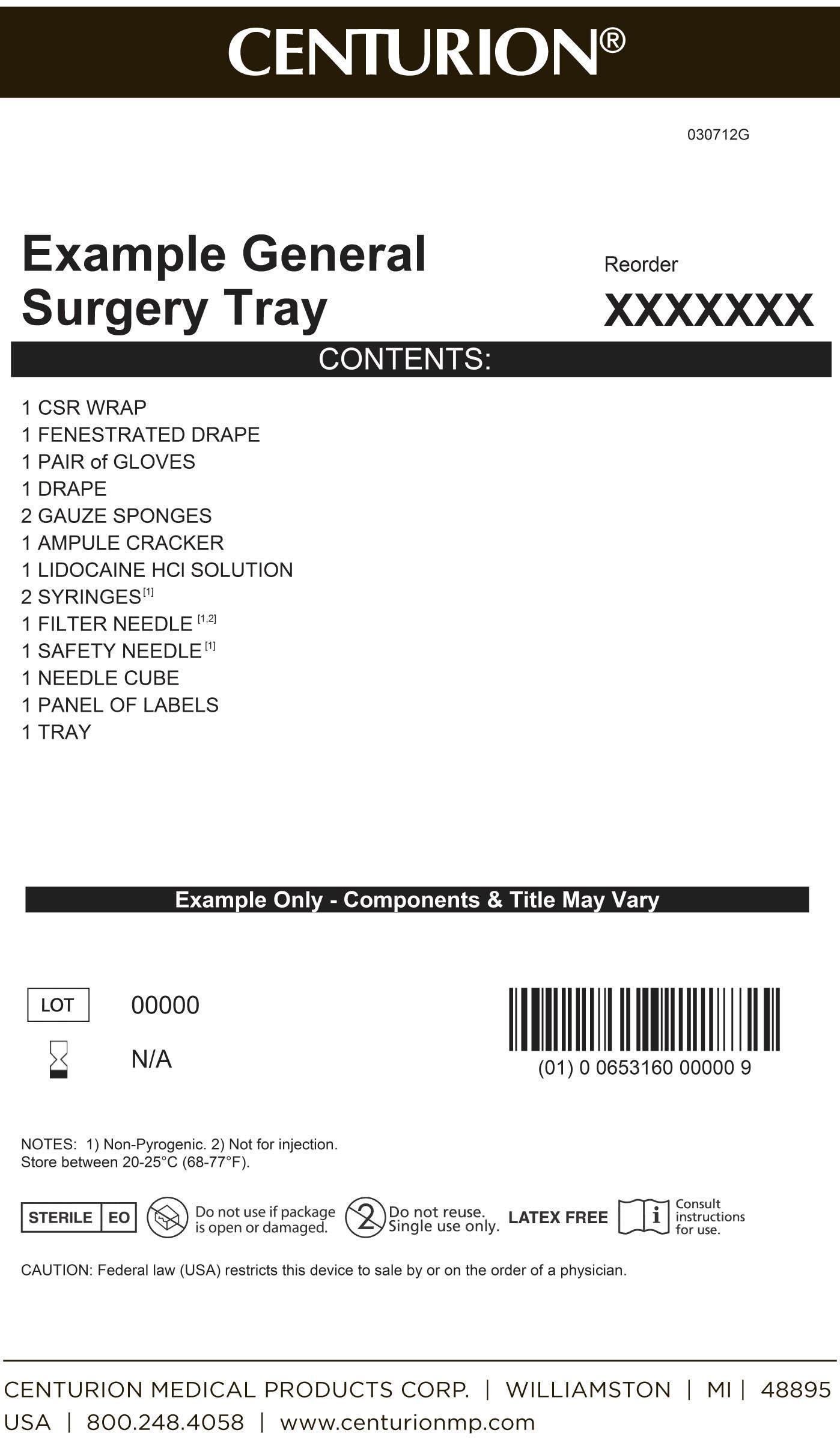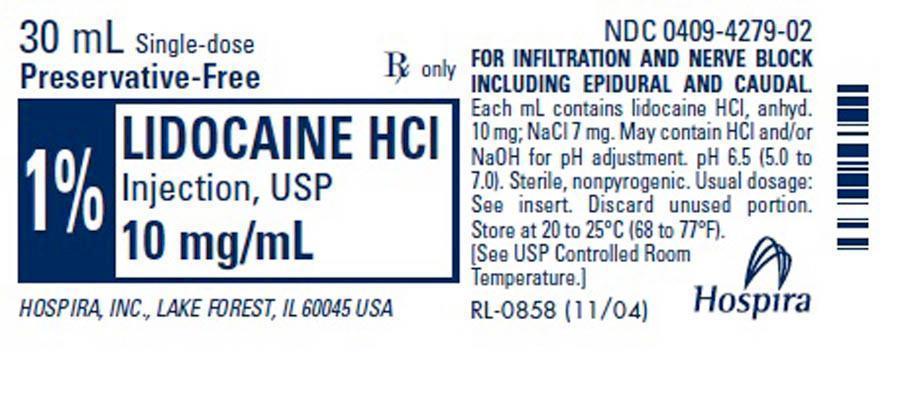 DRUG LABEL: General Surgery Procedure Kit
NDC: 24840-1509 | Form: KIT | Route: INFILTRATION
Manufacturer: Centurion Medical Products
Category: other | Type: MEDICAL DEVICE
Date: 20120921

ACTIVE INGREDIENTS: LIDOCAINE HYDROCHLORIDE ANHYDROUS 10 mg/1 mL
INACTIVE INGREDIENTS: SODIUM CHLORIDE 7 mg/1 mL; WATER; SODIUM HYDROXIDE; HYDROCHLORIC ACID

General Surgery Procedure Kit

DESCRIPTION

Lidocaine Hydrochloride Injection, USP is a sterile, nonpyrogenic solution of lidocaine hydrochloride in water for injection for parenteral administration in various concentrations. Multiple dose vials contain 0.1% of methylparaben added as preservative. Lidocaine is a local anesthetic of the amide type. The molecular weight is 288.82